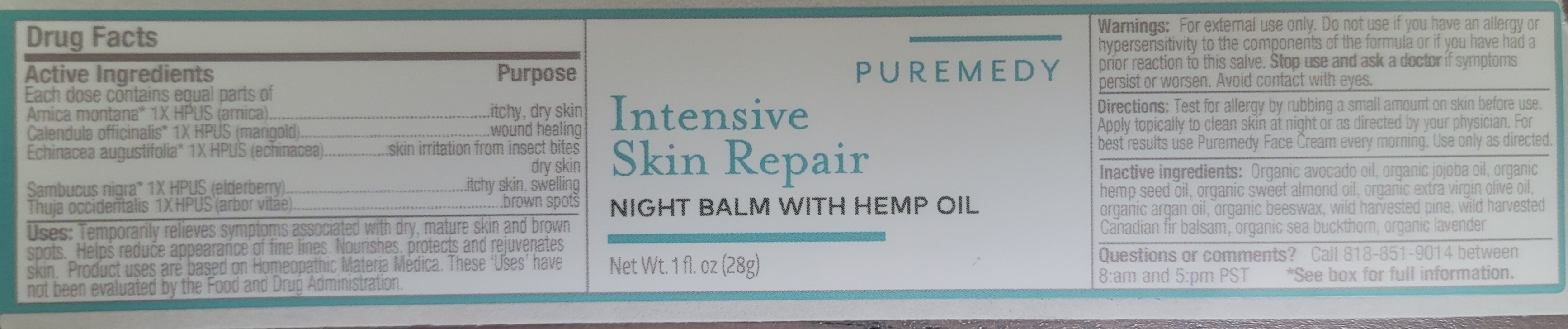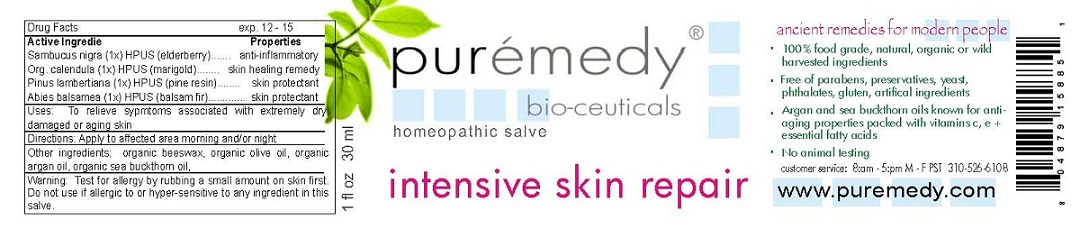 DRUG LABEL: INTENSIVE SKIN REPAIR
NDC: 52810-204 | Form: SALVE
Manufacturer: PUREMEDY
Category: homeopathic | Type: HUMAN OTC DRUG LABEL
Date: 20211006

ACTIVE INGREDIENTS: SAMBUCUS NIGRA FLOWER 1 [hp_X]/100 mL; CALENDULA OFFICINALIS FLOWER 1 [hp_X]/100 mL; PINUS LAMBERTIANA RESIN 1 [hp_X]/100 mL; ABIES BALSAMEA LEAF OIL 1 [hp_X]/100 mL
INACTIVE INGREDIENTS: OLIVE OIL; ARGAN OIL; YELLOW WAX; HIPPOPHAE RHAMNOIDES WHOLE

INTENSIVE SKIN REPAIR (52810-204)

ACTIVE INGREDIENTS

SAMBUCUS NIGRA (1X) HPUS (ELDERBERRY)

ORG. CALENDULA (1X) HPUS (MARIGOLD)

PINUS LAMBERTIANA (1X) HPUS (PINE RESIN)

ABIES BALSAMEA (1X) HPUS (BALSAM FIR)

PURPOSE

PROPERTIES

ANTI-INFLAMMATORY

SKIN HEALING REMEDY

SKIN PROTECTANT

SKIN PROTECTANT

INDICATIONS AND USAGE

USES: TO RELIEVE SYMPTOMS ASSOCIATED WITH EXTREMELY DRY, DAMAGED, OR AGING SKIN.

DOSAGE AND ADMINISTRATION

DIRECTIONS: APPLY TO AFFECTED AREA MORNING AND/OR NIGHT.

INACTIVE INGREDIENT

OTHER INGREDIENTS: ORGANIC BEESWAX, ORGANIC OLIVE OIL, ORGANIC ARGAN OIL, ORGANIC SEA BUCKTHORN OIL

WARNINGS

WARNING: TEST FOR ALLERGY BY RUBBING A SMALL AMOUNT ON SKIN FIRST. DO NOT USE IF ALLERGIC TO OR HYPER-SENSITIVE TO ANY INGREDIENT IN THIS SALVE. IF CONDITION PERSISTS OR WORSENS CONSULT YOUR HEALTH CARE PROVIDER. (* = CERTIFIED ORGANIC INGREDIENTS)

KEEP OUT OF REACH OF CHILDREN.

QUESTIONS

CUSTOMER SERVICE: 8:AM - 5:PM M - F 310-526-6108